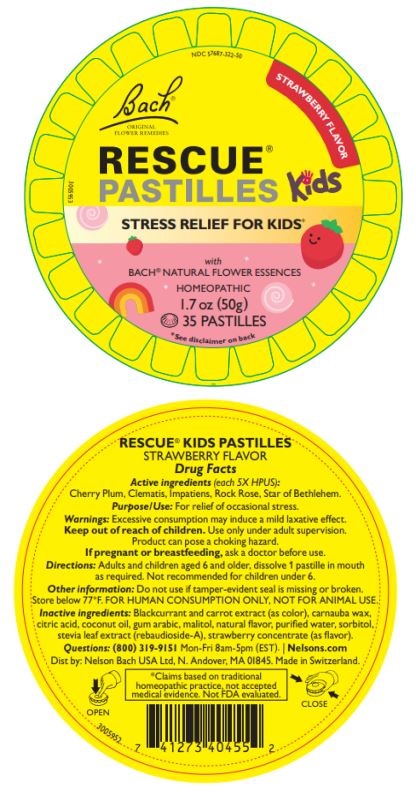 DRUG LABEL: RESCUE PASTILLES KIDS STRAWBERRY FLAVOR
NDC: 57687-322 | Form: LOZENGE
Manufacturer: Nelson Bach USA Ltd
Category: homeopathic | Type: HUMAN OTC DRUG LABEL
Date: 20250325

ACTIVE INGREDIENTS: ORNITHOGALUM UMBELLATUM FLOWERING TOP 5 [hp_X]/1 1; IMPATIENS GLANDULIFERA FLOWER 5 [hp_X]/1 1; PRUNUS CERASIFERA FLOWER 5 [hp_X]/1 1; HELIANTHEMUM NUMMULARIUM FLOWER 5 [hp_X]/1 1; CLEMATIS VITALBA FLOWER 5 [hp_X]/1 1
INACTIVE INGREDIENTS: BLACK CURRANT JUICE; CITRIC ACID MONOHYDRATE; ACACIA; STRAWBERRY JUICE; MALTITOL; CARROT JUICE; CARNAUBA WAX; WATER; STEVIOL; SORBITOL SOLUTION 70%

ACTIVE INGREDIENT

Active ingredients (each 5X HPUS): Cherry Plum, Clematis, Impatiens, Rock Rose, Star of Bethlehem

PURPOSE

For relief of occasional stress

INDICATIONS AND USAGE

For relief of occasional stress

Warnings

Excessive consumption may induce a mild laxative effect.

Keep out of reach of children. Use only under adult supervision. Product can pose a choking hazard.

PREGNANCY OR BREAST FEEDING

If pregnant or breastfeeding, ask a doctor before use.

DOSAGE AND ADMINISTRATION

Directions: Adults and children aged 6 and older, dissolve 1 pastille in mouth
as required. Not recommended for children under 6.

Do not use if tamper evident seal is missing or broken. Store below 77 F. For human consumption only, not for animal use.

INACTIVE INGREDIENT

Blackcurrant and carrot extract (as color), carnauba wax, citric acid, coconut oil, gum arabic, maltitol, natural flavor, purifed water, sorbitol, stevia leaf extract (rebaudioside-A), strawberry concentrate(as flavor).

QUESTIONS

Questions: (800) 319-9151 Mon-Fri 8am-5pm (EST).

Distributed by

Nelson Bach USA Ltd, N Andover, MA 01845